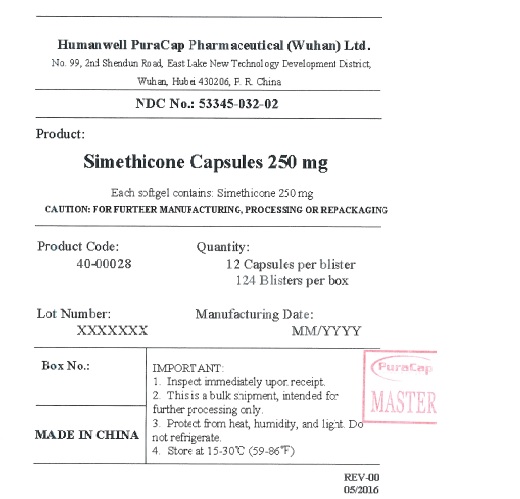 DRUG LABEL: Simethicone
NDC: 53345-032 | Form: CAPSULE, LIQUID FILLED
Manufacturer: Humanwell PuraCap Pharmaceutical (Wuhan) Co., Ltd
Category: otc | Type: HUMAN OTC DRUG LABEL
Date: 20241125

ACTIVE INGREDIENTS: DIMETHICONE 250 mg/1 1
INACTIVE INGREDIENTS: D&C RED NO. 33; FD&C BLUE NO. 1; GELATIN; GLYCERIN; WATER

Simethicone Capsules 250 mg

Drug Facts

Active ingredient (in each softgel)

Simethicone 250 mg

Purpose

Anti-gas

Use

relieves bloating, pressure or fullness commonly referred to as gas

Warnings

Stop use and ask a doctor if

condition persists

Keep out of reach of children.

Directions

- swallow one or two softgels after a meal
- do not exceed two softgels per 24 hours except under the advice and supervision of a physician

Other information

- store at room temperature 59°-86°F (15°-30°C)

Inactive ingredients

D&C red # 33, FD&C blue # 1, gelatin, glycerin, purified water and white edible ink

PRINCIPAL DISPLAY PANEL - Shipping Label

Simethicone Capsules 250 mg

NDC 53345-032-02

Quantity: 12 Capsules per blister

124 Blisters per box

IMPORTANT:

Inspect immediately upon receipt.
This is a bulk shipment, intended for further processing only.
Protect from heat, humidity, and light. Do not refrigerate.
Store at 15-30°C (59-86°F)
CAUTION : FOR FURTHER MANUFACTURING, PROCESSING OR REPACKAGING